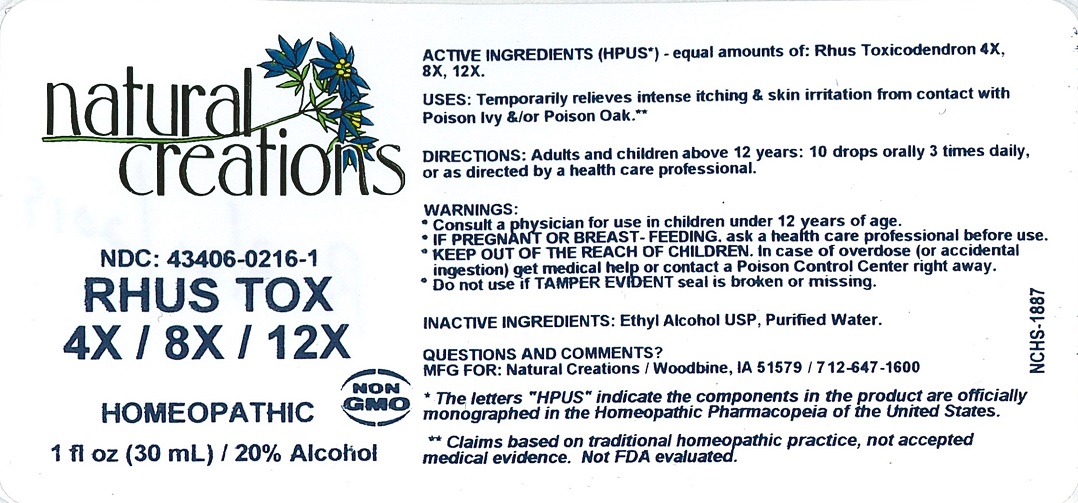 DRUG LABEL: Rhus Tox 4X / 8X / 12X
NDC: 43406-0216 | Form: LIQUID
Manufacturer: Natural Creations, Inc
Category: homeopathic | Type: HUMAN OTC DRUG LABEL
Date: 20251216

ACTIVE INGREDIENTS: TOXICODENDRON PUBESCENS LEAF 12 [hp_X]/1 mL
INACTIVE INGREDIENTS: ALCOHOL; WATER

RHUS TOX 4X/8X/12X

ACTIVE INGREDIENT

ACTIVE INGREDIENTS (HPUS) - equal amounts of: Rhus Toxicodendron 4X, 8X, 12X.

INDICATIONS AND USAGE

USES: Temporarily relieves intense itching & skin irritation from contact with Poison Ivy &/or Poison Oak.**

PURPOSE

USES: Temporarily relieves intense itching & skin irritation from contact with Poison Ivy &/or Poison Oak.**

DOSAGE AND ADMINISTRATION

DIRECTIONS: Adults and children above 12 years: 10 drops orally 3 times daily, or as directed by a health care professional.

KEEP OUT OF REACH OF CHILDREN

KEEP OUT OF THE REACH OF CHILDREN. In case of overdose (or accidental ingestion) get medical help or contact a Poison Control Center right away.

WARNINGS:

- Consult a physician for use in children under 12 years of age.
- IF PREGNANT OR BREAST-FEEDING, ask a health care professional before use.
- KEEP OUT OF THE REACH OF CHILDREN. In case of overdose (or accidental ingestion) get medical help or contact a Poison Control Center right away.
- Do not use if TAMPER EVIDENT seal is broken or missing.

INACTIVE INGREDIENTS: Ethyl Alcohol USP, Purified Water.

QUESTIONS & COMMENTS?

Natural Creations, Inc. / Woodbine, IA 51579 / 712-647-1600

REFERENCES

*The letters "HPUS" indicate the components in the products are officially monographed in the Homeopathic Pharmacopeia of the United States.

**Claims based on traditional homeopathic practice, not accepted medical evidence. Not FDA evaluated.

PACKAGE LABEL

NDC: 43406-0216-1

RHUS TOX 4X / 8X / 12X

Homeopathic

1 fl oz (30 mL) / 20% Alcohol